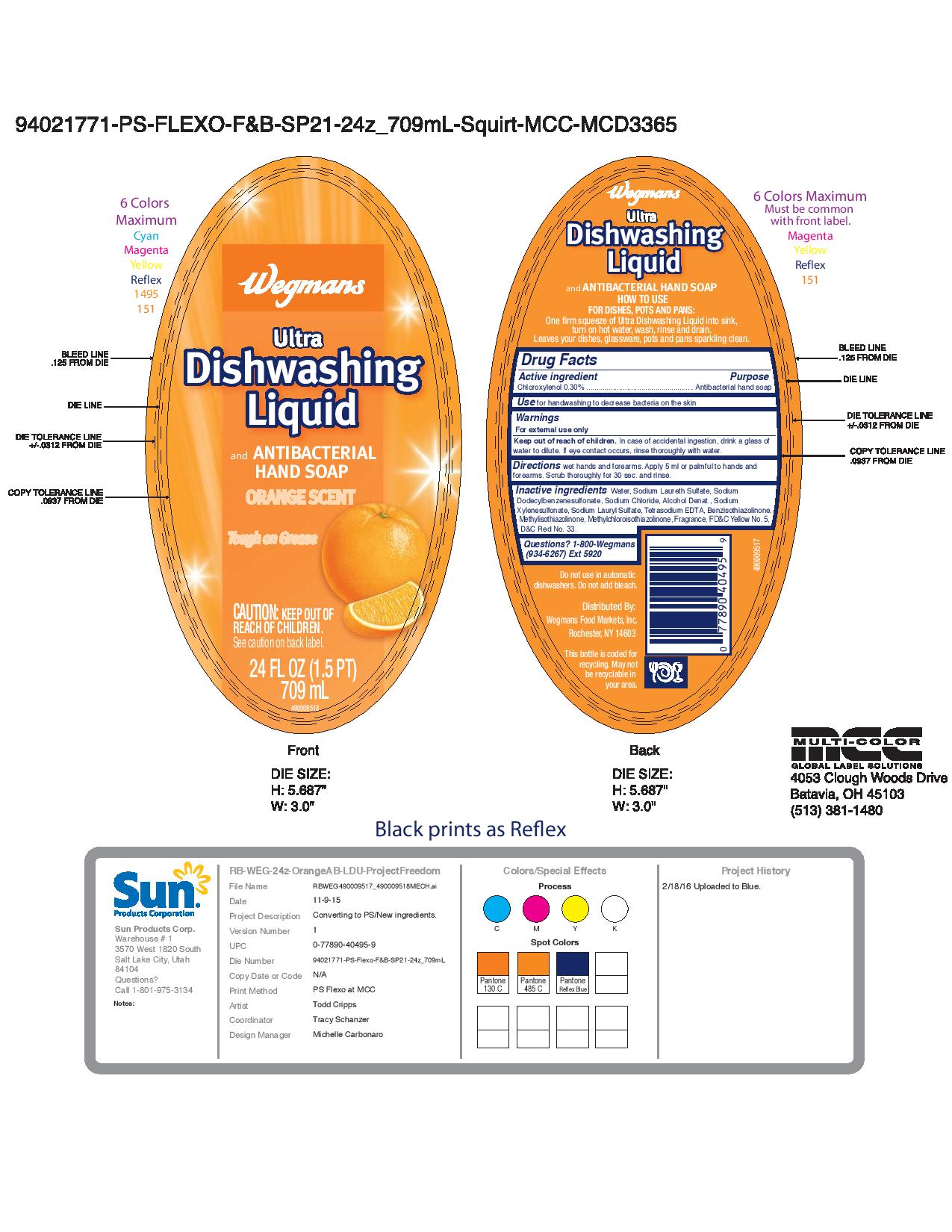 DRUG LABEL: Wegmans Ultra Dishwashing Liquid Orange
NDC: 54340-501 | Form: SOAP
Manufacturer: Henkel Corporation
Category: otc | Type: HUMAN OTC DRUG LABEL
Date: 20190114

ACTIVE INGREDIENTS: CHLOROXYLENOL 0.3 g/100 mL
INACTIVE INGREDIENTS: ALCOHOL; SODIUM XYLENESULFONATE; SODIUM LAURYL SULFATE; EDETATE SODIUM; BENZISOTHIAZOLINONE; METHYLISOTHIAZOLINONE; FD&C YELLOW NO. 5; D&C RED NO. 33; SODIUM CHLORIDE; WATER; METHYLCHLOROISOTHIAZOLINONE; SODIUM LAURETH-3 SULFATE; SODIUM DODECYLBENZENESULFONATE

Wegmans Ultra Dishwashing Liquid Orange

Active ingredient Chloroxylenol 0.30%

PURPOSE

Antibacterial hand soap

Warnings For external use only

INDICATIONS AND USAGE

Use for handwashing to decrease bacteria on the skin

Keep out of reach of children. In case of accidental ingestion, drink a glass of water to dilute. If eye contact occurs, rinse thoroughly with water.

DOSAGE AND ADMINISTRATION

Directions wet hands and forearms. Apply 5 mL or palmful to hands and forearms. Scrub thoroughly for 30 sec. and rinse.

INACTIVE INGREDIENT

Inactive ingredients Water, Sodium Laureth Sulfate, Sodium Dodecylbenzenesulfonate, Sodium Chloride, Alcohol Denat., Sodium Xylenesulfonate, Sodium Tetrasodium EDTA, Benzisothiazolinone, Methylisothiazolinone, Methylchloroisothiazolinone, Fragrance, FD&C Yellow No. 5, D&C Red No. 33.

Questions? 1-800-Wegmans (934-6267) Ext 5920